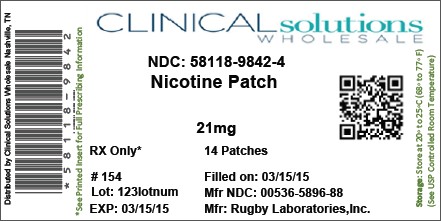 DRUG LABEL: Nicotine
NDC: 58118-9842 | Form: PATCH
Manufacturer: Clinical Solutions Wholesale
Category: otc | Type: HUMAN OTC DRUG LABEL
Date: 20131201

ACTIVE INGREDIENTS: Nicotine 21 mg/24 h
INACTIVE INGREDIENTS: dimethicone

Drug Facts

Active ingredient (in each patch)

Nicotine, 21 mg delivered over 24 hours

Purpose

Stop smoking aid

Uses

Reduces withdrawal symptoms, including nicotine craving, associated with quitting smoking

Warnings

PREGNANCY OR BREAST FEEDING

If you are pregnant or breast-feeding, only use this medicine on the advice of your health care provider. Smoking can seriously harm your child. Try to stop smoking without using any nicotine replacement medicine. This medicine is believed to be safer than smoking. However, the risks to your child from this medicine are not fully known.

Do not use

- If you continue to smoke, chew tobacco, use snuff, use nicotine gum, or use nicotine patch or other nicotine-containing products

Ask a doctor before use if you have

- Heart disease, recent heart attack, or irregular heartbeat. Nicotine can increase your heart rate.
- High blood pressure not controlled with medication. Nicotine can increase your blood pressure.
- An allergy to adhesive tape or skin problems because you are more likely to get rashes

Ask a doctor or pharmacist before use if you are

- Using a non-nicotine stop smoking drug
- Taking a prescription medicine for depression or asthma. Your prescription dose may need to be adjusted.

When using this product

- Do not smoke even when not wearing the patch. The nicotine in your skin will still be entering your bloodstream for several hours after you take off the patch.
- If you have vivid dreams or other sleep disturbances, remove this patch at bedtime

Stop use and ask a doctor if

- Skin redness caused by the patch does not go away after four days, or your skin swells, or you get a rash
- Irregular heartbeat or palpitations occur
- You get symptoms of nicotine overdose, such as nausea, vomiting, dizziness, weakness, and rapid heartbeat

Keep out of reach of children and pets

Used patches have enough nicotine to poison children and pets. If swallowed, get medical help or contact a Poison Control Center right away. Save pouch to use for patch disposal. Dispose of used patch by folding sticky ends together and putting in pouch.

Directions

- If you are under 18 years of age, ask a doctor before use
- Before using this product, read the enclosed self-help guide for complete directions and other information
- Stop smoking completely when you begin using the patch
- If you smoke more than 10 cigarettes per day, use the following schedule:

Weeks 1 thru 4 | Weeks 5 and 6 | Weeks 7 and 8
STEP 1 | STEP 2 | STEP 3
use one 21 mg patch/day | use one 14 mg patch/day | use one 7 mg patch/day

- If you smoke 10 or less cigarettes per day, start with Step 2 for 6 weeks, then Step 3 for 2 weeks and then stop
- Apply one new patch every 24 hours on skin that is dry, clean, and hairless
- Remove backing from patch and immediately press onto skin. Hold for 10 seconds.
- Wash hands after applying or removing patch. Save pouch to use for patch disposal. Dispose of used patch by folding sticky ends together and putting in pouch.
- The used patch should be removed and a new one applied to a different skin site at the same time each day
- If you have vivid dreams, you may remove the patch at bedtime and apply a new one in the morning
- Do not wear more than one patch at a time
- Do not cut patch in half or into smaller pieces
- Do not leave patch on for more than 24 hours because it may irritate your skin and loses strength after 24 hours
- Stop using the patch at the end of 8 weeks. If you still feel the need to use the patch talk to your doctor.

Other information

Store at 20°-25°C (68°-77°F)

Inactive ingredients

acrylate adhesive, polyester, silicone adhesive

Comments or questions?

Call-1-877-440-7867 8 AM - 8PM ET, Monday-Friday

This product is not affiliated with Novartis Consumer Health, Inc.

PACKAGE LABEL

Principal Display Panel - Step 1 – 21 mg Carton Label

Rugby®

NDC 0536-5896-88

COMPARE TO THE ACTIVE INGREDIENT IN HABITROL®*

Clear

Nicotine

Transdermal System

21 mg delivered over 24 hours

STOP SMOKING AID

21 mg

Includes Behavior Support Program with Self-Help Guide

Free Audio CD upon request.

STEP ONE

If you smoke MORE than 10 cigarettes per day: Start with Step 1

If you smoke 10 or LESS cigarettes per day: Start with Step 2

14 Patches

*Habitrol® is a registered trademark of Novartis Consumer Health, Inc.